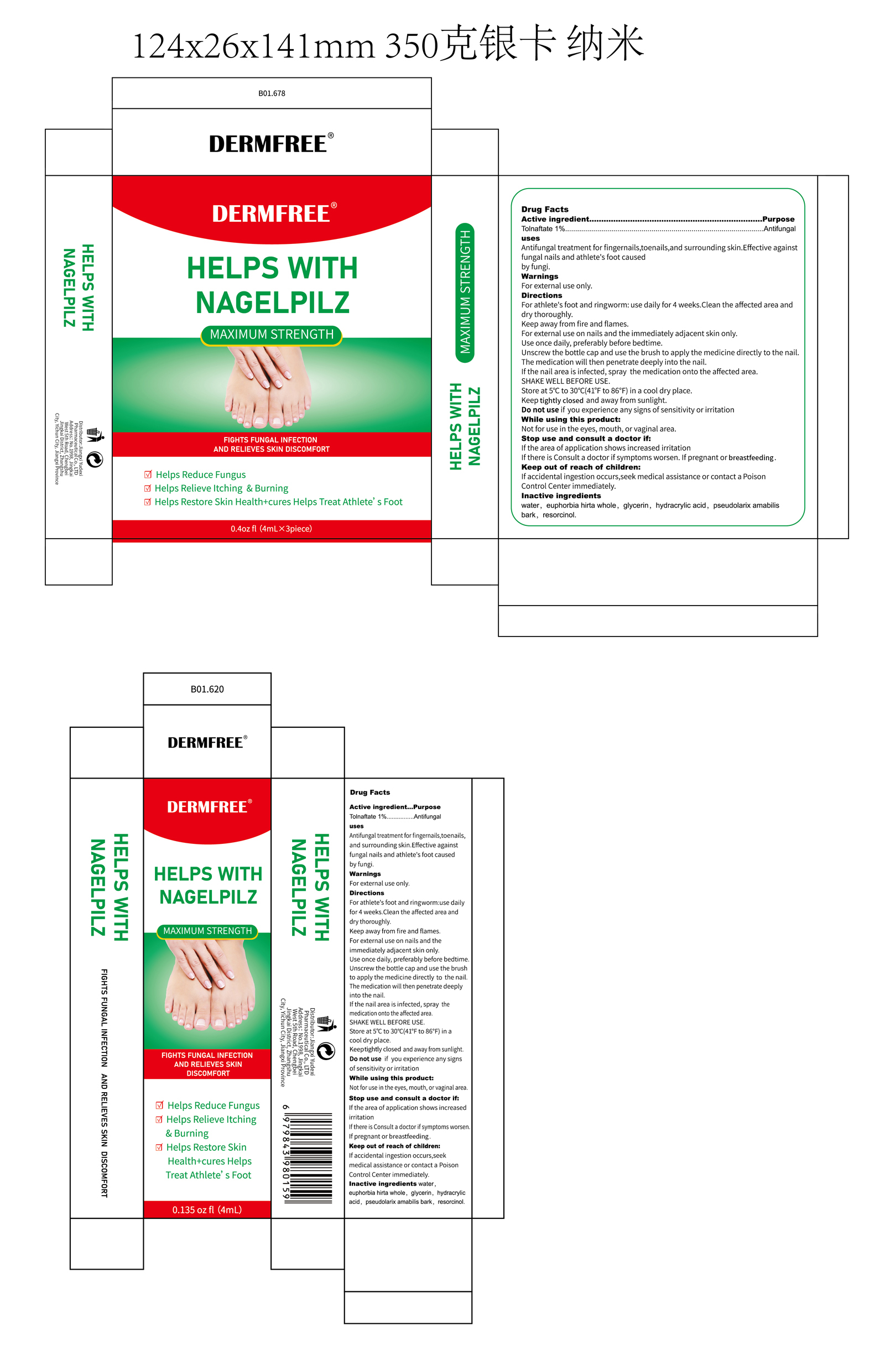 DRUG LABEL: DERMFREE  HELPS WITH NAGELPILZ
NDC: 85248-115 | Form: LIQUID
Manufacturer: Jiangxi Yudexi Pharmaceutical Co., LTD
Category: otc | Type: HUMAN OTC DRUG LABEL
Date: 20260208

ACTIVE INGREDIENTS: TOLNAFTATE 1 g/100 mL
INACTIVE INGREDIENTS: WATER; GLYCERIN; EUPHORBIA HIRTA WHOLE; PSEUDOLARIX AMABILIS BARK; HYDRACRYLIC ACID; RESORCINOL

85248-115

Active Ingredient

Tolnaftate 1%

Purpose

Antifungal

Use

Antifungal treatment for fingernails,toenails, and surrounding skin.Effective against fungal nails and athlete's foot caused by fungi.

Warnings

For external use only.

Do not use

if you experience any signs of sensitivity or irritation

When Using

Not for use in the eyes, mouth,or vaginal area.

Stop Use

If the area of application shows increased irritation
If there is Consult a doctor if symptoms worsen.If pregnant or breastfeeding

Ask Doctor

If the area of application shows increased irritation
If there is Consult a doctor if symptoms worsen.If pregnant or breastfeeding

Keep Oot Of Reach Of Children

If accidental ingestion occurs,seek medical assistance or contact a Poison Control Center immediately.

Directions

For athlete's foot and ringworm：use daily for 4 weeks.Clean the affected area and dry thoroughly.Keep away from fire and flames.For external use on nails and the immediately adjacent skin only.Use once daily, preferably before bedtime.
Unscrew the bottle cap and use the brush to apply the medicine directly to the nail.The medication will then penetrate deeply into the nail.If the nail area is infected, spray the medication onto the affected area.SHAKE WELL BEFORE USE.Store at 5'c to 30°0(41'F to 86°F) in a cool dry place. Keep tightly closed and away from sunlight

Inactive ingredients

water，euphorbia hirta whole, glycerin，hydracrylic acid, pseudolarix amabilis bark, resorcinol.